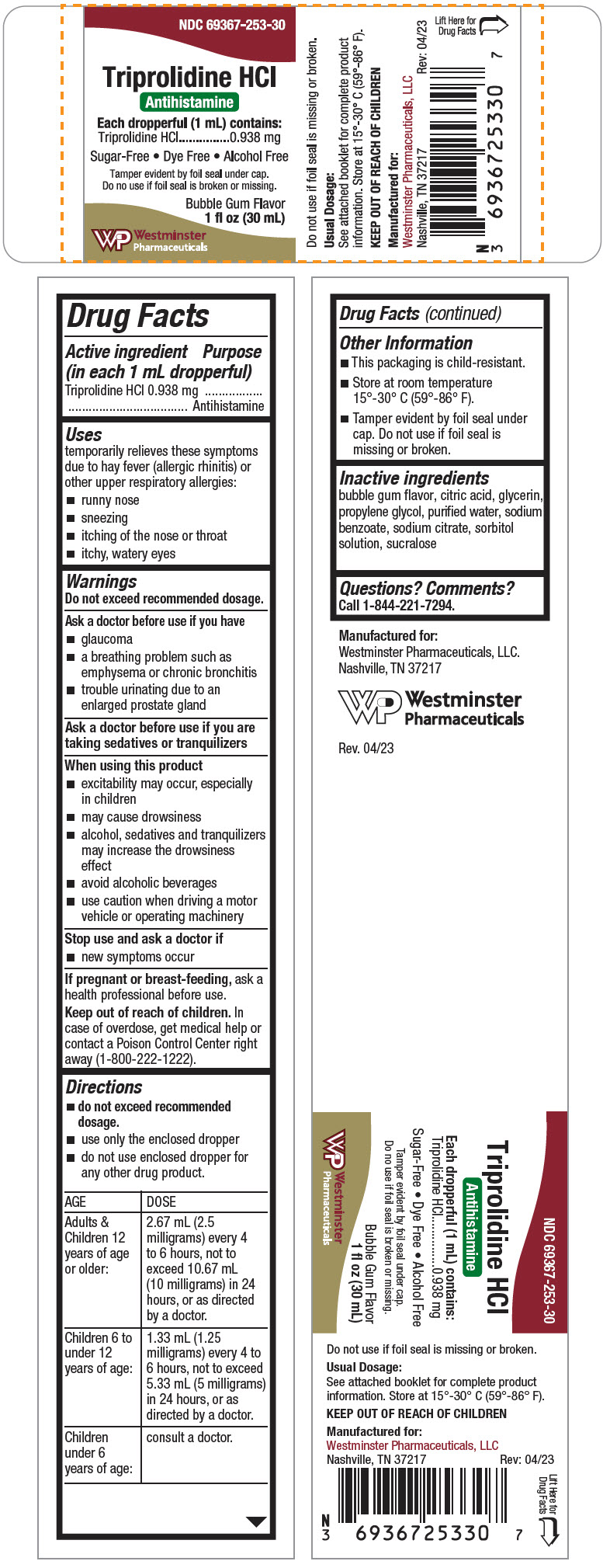 DRUG LABEL: TRIPROLIDINE HYDROCHLORIDE
NDC: 69367-253 | Form: SYRUP
Manufacturer: Westminster Pharmaceuticals, LLC
Category: otc | Type: HUMAN OTC DRUG LABEL
Date: 20200501

ACTIVE INGREDIENTS: TRIPROLIDINE HYDROCHLORIDE 0.938 mg/1 mL
INACTIVE INGREDIENTS: CITRIC ACID MONOHYDRATE; GLYCERIN; PROPYLENE GLYCOL; WATER; SUCRALOSE; SODIUM BENZOATE; SODIUM CITRATE, UNSPECIFIED FORM; SORBITOL

Triprolidine HCl

Drug Facts

Active ingredient (in each 1 mL dropperful)

Triprolidine HCl 0.938 mg

Purpose

Antihistamine

Uses

temporarily relieves these symptoms due to hay fever (allergic rhinitis) or other upper respiratory allergies:

- runny nose
- sneezing
- itching of the nose or throat
- itchy, watery eyes

Warnings

Do not exceed recommended dosage.

Ask a doctor before use if you have

- glaucoma
- a breathing problem such as emphysema or chronic bronchitis
- trouble urinating due to an enlarged prostate gland

Ask a doctor before use if you are taking sedatives or tranquilizers

When using this product

- excitability may occur, especially in children
- may cause drowsiness
- alcohol, sedatives and tranquilizers may increase the drowsiness effect
- avoid alcoholic beverages
- use caution when driving a motor vehicle or operating machinery

Stop use and ask a doctor if

- new symptoms occur

PREGNANCY OR BREAST FEEDING

If pregnant or breast-feeding, ask a health professional before use.

Keep out of reach of children. In case of overdose, get medical help or contact a Poison Control Center right away (1-800-222-1222).

Directions

- do not exceed recommended dosage.
- use only the enclosed dropper
- do not use enclosed dropper for any other drug product.

AGE | DOSE
Adults & Children 12 years of age or older: | 2.67 mL (2.5 milligrams) every 4 to 6 hours, not to exceed 10.67 mL (10 milligrams) in 24 hours, or as directed by a doctor.
Children 6 to under 12 years of age: | 1.33 mL (1.25 milligrams) every 4 to 6 hours, not to exceed 5.33 mL (5 milligrams) in 24 hours, or as directed by a doctor.
Children under 6 years of age: | consult a doctor.

Other Information

- This packaging is child-resistant.
- Store at room temperature 15°-30° C (59°-86° F).
- Tamper evident by foil seal under cap. Do not use if foil seal is missing or broken.

Inactive ingredients

bubble gum flavor, citric acid, glycerin, propylene glycol, purified water, sodium benzoate, sodium citrate, sorbitol solution, sucralose

Questions? Comments?

Call 1-844-221-7294.

PRINCIPAL DISPLAY PANEL - 30 mL Bottle Carton

NDC 69367-253-30

Triprolidine HCl
Antihistamine
Each dropperful (1 mL) contains:
Triprolidine HCl 0.938 mg

Sugar-Free • Dye Free • Alcohol Free

Tamper evident by foil seal under cap.
Do no use if foil seal is broken or missing.

Bubble Gum Flavor
1 fl oz (30 mL)

Westminster
Pharmaceuticals